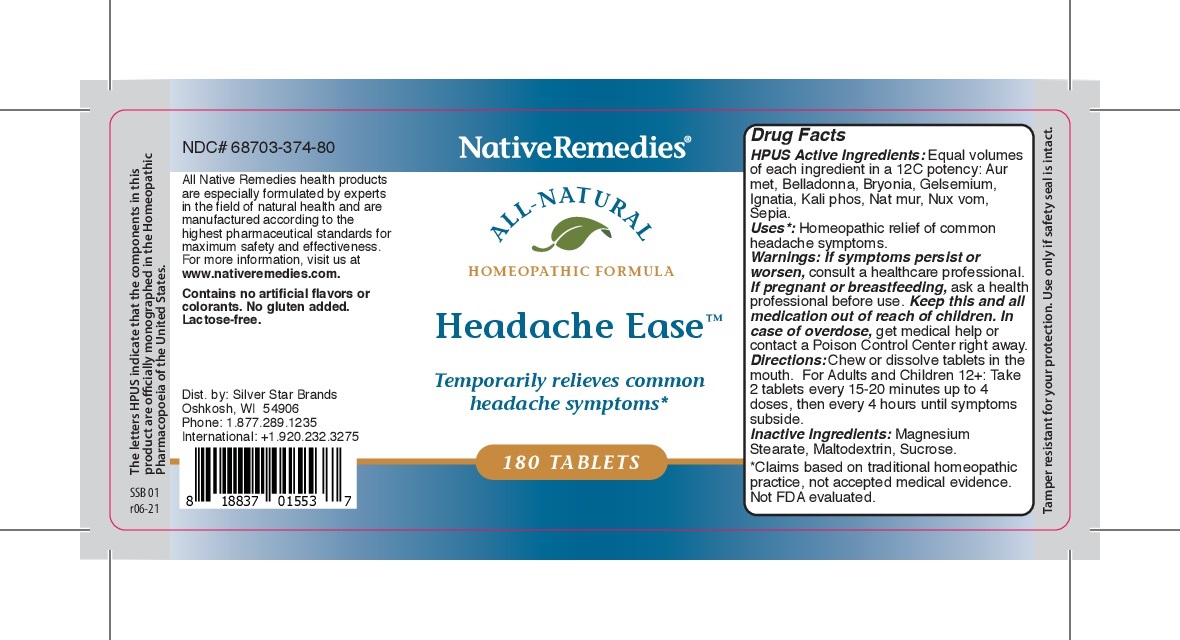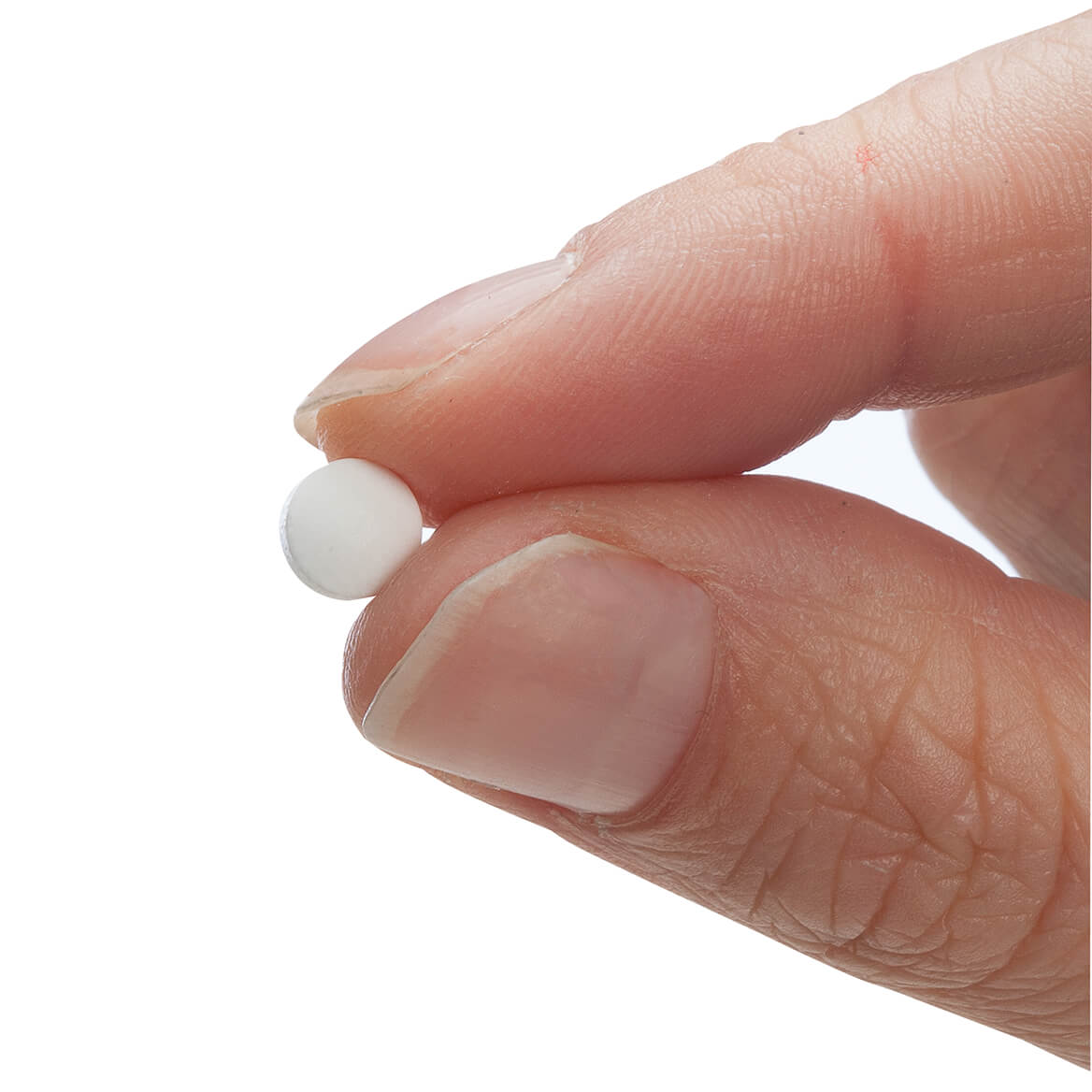 DRUG LABEL: Headache Ease
NDC: 68703-374 | Form: TABLET
Manufacturer: Silver Star Brands
Category: homeopathic | Type: HUMAN OTC DRUG LABEL
Date: 20250101

ACTIVE INGREDIENTS: STRYCHNOS NUX-VOMICA SEED 12 [hp_C]/180 1; POTASSIUM PHOSPHATE, DIBASIC 12 [hp_C]/180 1; SEPIA OFFICINALIS JUICE 12 [hp_C]/180 1; ATROPA BELLADONNA 12 [hp_C]/180 1; GOLD 12 [hp_C]/180 1; GELSEMIUM SEMPERVIRENS ROOT 12 [hp_C]/180 1; STRYCHNOS IGNATII SEED 12 [hp_C]/180 1; BRYONIA ALBA ROOT 12 [hp_C]/180 1; SODIUM CHLORIDE 12 [hp_C]/180 1
INACTIVE INGREDIENTS: MAGNESIUM STEARATE; MALTODEXTRIN; SUCROSE

NativeRemedies® Headache Ease Tablets

HPUS Active Ingredients: Equal volumes of each ingredient in a 12C potency: Aur met, Belladonna, Bryonia, Gelsemium, Ignatia, Kali phos, Nat mur, Nux vom, Sepia.

Uses*

Uses*: Homeopathic relief of common headache symptoms.

Warnings

Warnings: If symptoms persist or worsen, consult a healthcare professional. If pregnant or breastfeeding, ask a health professional before use. Keep this and all medication out of reach of children. In case of overdose, get medical help or contact a Poison Control Center.

Directions

Directions: Chew or dissolve tablets int he mouth. For Adults and Children 12+: Take 2 tablets every 15-20 minutes up to 4 doses, then every 4 hours until symptoms subside.

OTHER SAFETY INFORMATION

Contains no artificial flavors or colorants. No gluten added. Lactose-free.

Tamper resistant for your protection. Use only if safety seal is intact.

Inactive Ingredients

Inactive Ingredients: Magnesium Stearate, Maltodextrin, Sucrose.

KEEP OUT OF REACH OF CHILDREN

Keep this and all medication out of reach of children.

PREGNANCY OR BREAST FEEDING

If pregnant or breastfeeding, ask a health professional before use.

PURPOSE

Temporarily relieves common headache symptoms*

*Claims based on traditional homeopathic practice, not accepted medical evidence. Not FDA evaluated.